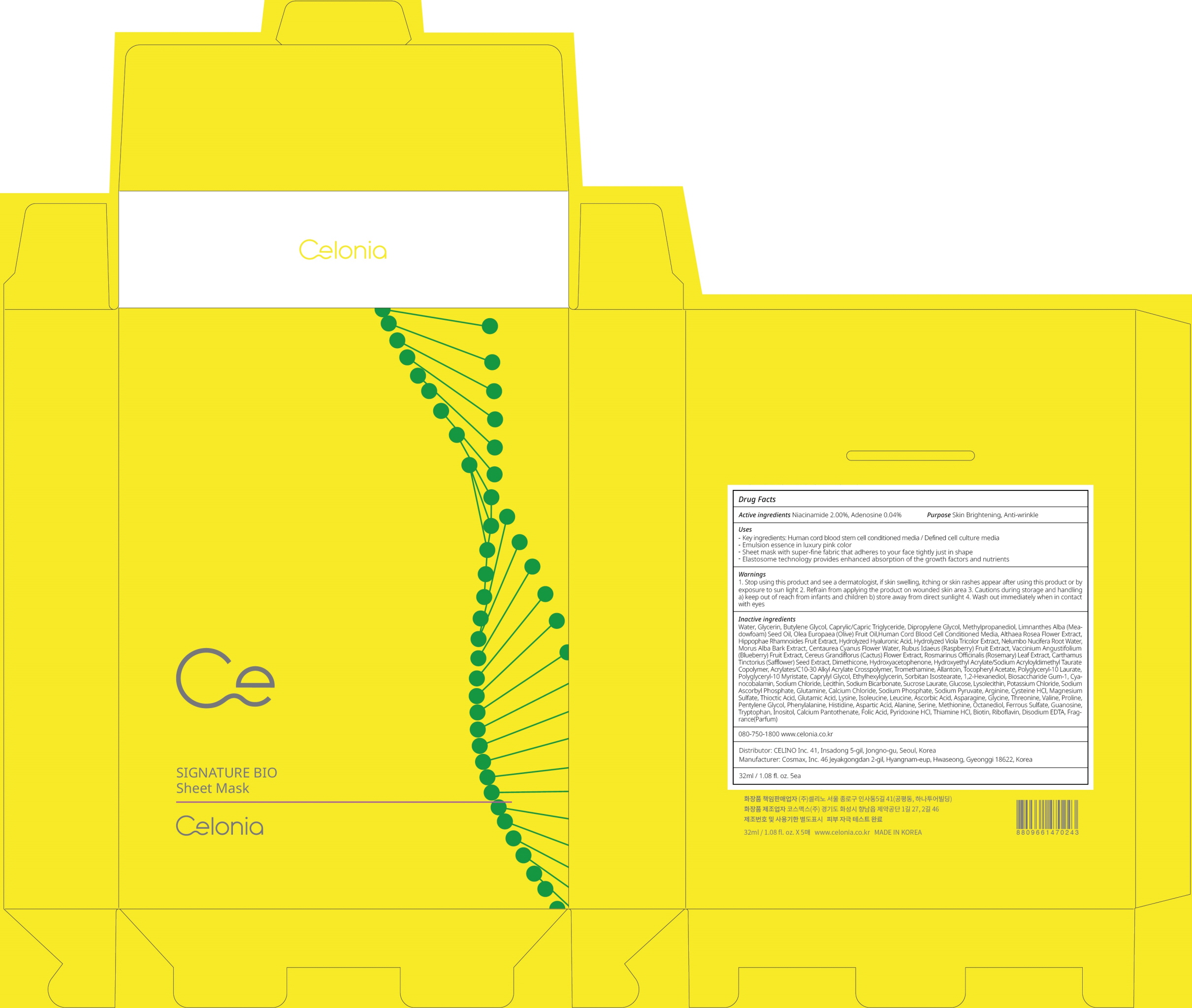 DRUG LABEL: CELONIA SIGNATURE BIO SHEET MASK
NDC: 73655-050 | Form: PATCH
Manufacturer: Celino Inc.
Category: otc | Type: HUMAN OTC DRUG LABEL
Date: 20200310

ACTIVE INGREDIENTS: Niacinamide 0.64 g/32 mL; Adenosine 0.01 g/32 mL
INACTIVE INGREDIENTS: Water; Glycerin

ACTIVE INGREDIENT

Active ingredients: Niacinamide 2.00%, Adenosine 0.04%

INACTIVE INGREDIENT

Inactive ingredients:

Water,Glycerin,Butylene Glycol,Caprylic/Capric Triglyceride, Dipropylene Glycol,Methylpropanediol,Limnanthes Alba (Meadowfoam) Seed Oil,Olea Europaea (Olive) Fruit Oil,Human Cord Blood Cell Conditioned Media,Althaea Rosea Flower Extract,Hippophae Rhamnoides Fruit Extract,Hydrolyzed Hyaluronic Acid,Hydrolyzed Viola Tricolor Extract,Nelumbo Nucifera Root Water,Morus Alba Bark Extract,Centaurea Cyanus Flower Water,Rubus Idaeus (Raspberry) Fruit Extract,Vaccinium Angustifolium (Blueberry) Fruit Extract,Cereus Grandiflorus (Cactus) Flower Extract,Rosmarinus Officinalis (Rosemary) Leaf Extract,Carthamus Tinctorius (Safflower) Seed Extract,Dimethicone,Hydroxyacetophenone,Hydroxyethyl Acrylate/Sodium Acryloyldimethyl Taurate Copolymer,Acrylates/C10-30 Alkyl Acrylate Crosspolymer,Tromethamine,Allantoin,Tocopheryl Acetate,Polyglyceryl-10 Laurate,Polyglyceryl-10 Myristate,Caprylyl Glycol,Ethylhexylglycerin,Sorbitan Isostearate,1,2-Hexanediol,Biosaccharide Gum-1,Cyanocobalamin,Sodium Chloride,Lecithin,Sodium Bicarbonate,Sucrose Laurate,Glucose,Lysolecithin,Potassium Chloride,Sodium Ascorbyl Phosphate,Glutamine,Calcium Chloride,Sodium Phosphate,Sodium Pyruvate,Arginine,Cysteine HCl,Magnesium Sulfate,Thioctic Acid,Glutamic Acid,Lysine,Isoleucine,Leucine,Ascorbic Acid,Asparagine,Glycine,Threonine,Valine,Proline,Pentylene Glycol,Phenylalanine,Histidine,Aspartic Acid,Alanine,Serine,Methionine,Octanediol,Ferrous Sulfate,Guanosine,Tryptophan,Inositol,Calcium Pantothenate,Folic Acid,Pyridoxine HCl,Thiamine HCl,Biotin,Riboflavin,Disodium EDTA,Fragrance(Parfum)

PURPOSE

Purpose: Skin Brightening, Anti-wrinkle

WARNINGS

1. Stop using this product and see a dermatologist, if skin swelling, itching or skin rashes appear after using this product or by exposure to sun light

2. Refrain from applying the product on wounded skin area

3. Cautions during storage and handling a) keep out of reach from infants and children b) store away from direct sunlight

4. Wash out immediately when in contact with eyes

KEEP OUT OF REACH OF CHILDREN

keep out of reach from infants and children

QUESTIONS

080-750-1800

www.celonia.co.kr

Uses

Key ingredients: Human cord blood stem cell conditioned media / Defined cell culture media
Emulsion essence in luxury pink color
Sheet mask with super-fine fabric that adheres to your face tightly just in shape
Elastosome technology provides enhanced absorption of the growth factors and nutrients

Directions

Gently dry your face after cleansing and put the sheet mask evenly over your face. 2. Detach the sheet mask after 10~20 minutes of Cell Training. 3. Gently pat the remaining emulsion essence for absorption.